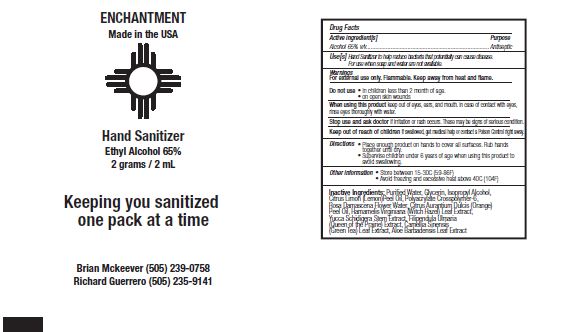 DRUG LABEL: ENCHANTMENT HAND SANITIZER
NDC: 61577-1119 | Form: GEL
Manufacturer: SOMBRA COSMETICS
Category: otc | Type: HUMAN OTC DRUG LABEL
Date: 20201106

ACTIVE INGREDIENTS: ALCOHOL 65 mL/100 mL
INACTIVE INGREDIENTS: WATER; GLYCERIN; ISOPROPYL ALCOHOL; LEMON PEEL; ORANGE OIL; AMMONIUM ACRYLOYLDIMETHYLTAURATE, DIMETHYLACRYLAMIDE, LAURYL METHACRYLATE AND LAURETH-4 METHACRYLATE COPOLYMER, TRIMETHYLOLPROPANE TRIACRYLATE CROSSLINKED (45000 MPA.S); ROSA DAMASCENA FLOWER; WITCH HAZEL; YUCCA SCHIDIGERA STEM; FILIPENDULA ULMARIA WHOLE; GREEN TEA LEAF; ALOE VERA LEAF

Enchantment Hand Sanitizer

Active Ingredients

Alcohol 65%

Uses

Helps reduce bacteria on the skin that potentially can cause disease. For use when soap and water are not available.

Warnings

Flammable. Keep away from heat and flame. For external use only.

Do not use

In children less than 2 months of age. On open skin wounds

When Using

When using this product, keep out of eyes, ears and mouth. In case of contact with eyes, rinse eyes thoroughly with water.

Stop use and ask a doctor if irritation or rash occurs. These may be signs of serious condition.

Keep out of reach of children. If swallowed, get medical help or contact a Poison Control Center right away.

Directions

Place enough product on hands to cover all surfaces. Rub hands together until dry. Supervise children under 6 years of age when using this product to avoid swallowing.

Storage

Store between 15-30C (59-86F)
Avoid freezing and excessive heat above 40C (104F)

Inactive ingredients

glycerin, purified water, isopropyl alcohol, polyacrylate crosspolymer-6, citrus limon (lemon) peel oil, citrus aurantium dulcis (orange) peel oil, yucca schidigera stem extract, rosa damascena flower water, hamamelis virginiana (witch hazel) leaf extract, filipendula ulmaria (queen of the prairie) extract, camellia sinensis (green tea) leaf extract, aloe barbadensis leaf extract.

*organic

Purpose

Antiseptic